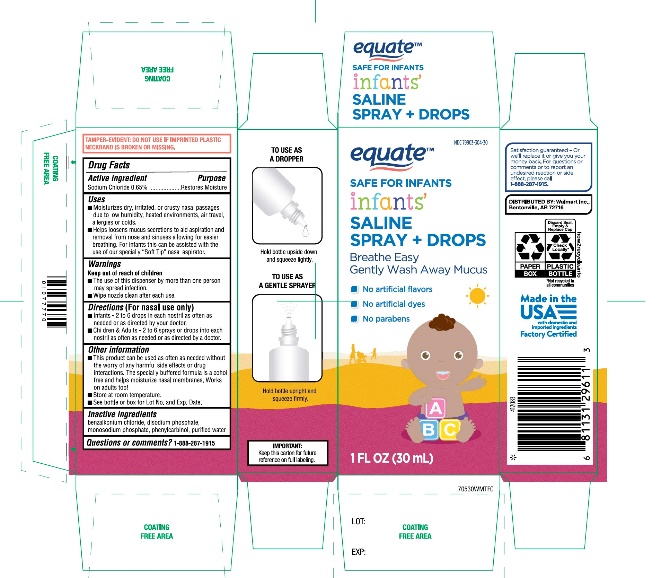 DRUG LABEL: WALMART

NDC: 79903-304 | Form: SPRAY
Manufacturer: WALMART STORES INC
Category: otc | Type: HUMAN OTC DRUG LABEL
Date: 20251028

ACTIVE INGREDIENTS: SODIUM CHLORIDE 6.5 mg/1 mL
INACTIVE INGREDIENTS: BENZALKONIUM CHLORIDE; SODIUM PHOSPHATE, DIBASIC, UNSPECIFIED FORM; SODIUM PHOSPHATE, MONOBASIC, ANHYDROUS; BENZYL ALCOHOL; WATER

Walmart Saline Spray + Drops 1 FL OZ

Active Ingredient: Sodium Chloride 0.65%

Purpose

Restores Moisture

Uses

- Moisturizes dry, irritated, or crusty nasal passages due to low humidity, heated environments, air travel, allergies or colds.
- Helps loosens mucus secretions to aid aspiration and removal from nose and sinuses allowing for easier breathing. For newborns/infant this can be assisted with the use of our specially soft tip nasal Aspirator

Warnings

Directions (For nasal use only)

- Newborns/ Infants- 2 to 6 drops in each nostril as often as needed or as directed by your doctor.
- Children & Adults-2 to 6 Sprays /drops into each nostril as often as needed or as directed by a doctor.

Other Information

- This product is non-medicated and can be used as often as needed without the worry of any harmful side effects or drug interactions. The specially buffered formula is alcohol free and helps moisturize nasal membranes. Works on adult too!
- Store at room temperature
- See bottle or box for Lot No. and Exp. Date

Warnings

-
  -
    - The use of this dispenser by more than one person may spread infection
    - Wipe nozzle clean after each use

Keep Out of Reach of Children

INACTIVE INGREDIENT

Other Ingredients
benzalkonium chloride, disodium phosphate, monosodium phosphate, phenylcarbinol, Purified Water

Questions or comments?

1-866-467-2748

PACKAGE LABEL

NDC 79903-304-30

SAFE FOR NEWBORNS

SALINE SPRAY + DROPS

Beathe Easy

Gently Wash Away Mucus

- No Artificial Flavors
- No Artificial Dyes
- No Parabens

1 FL OZ (30 mL)

To use as a dropper:

Hold bottle upside down and squeeze lightly.

To use as a gentle sprayer:

Hold bottle upright and squeeze firm.

DO NOT USE IF IMPRINTED PLASTIC NECKBAND IS BROKEN OR MISSING

Distributed by: